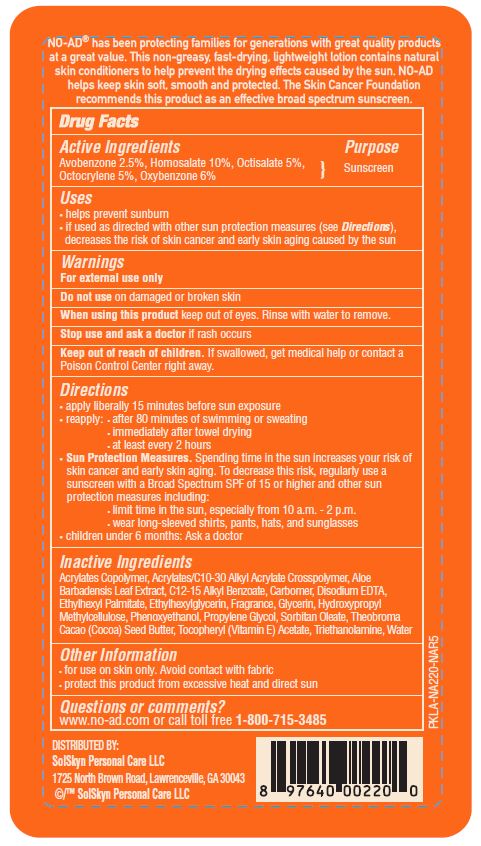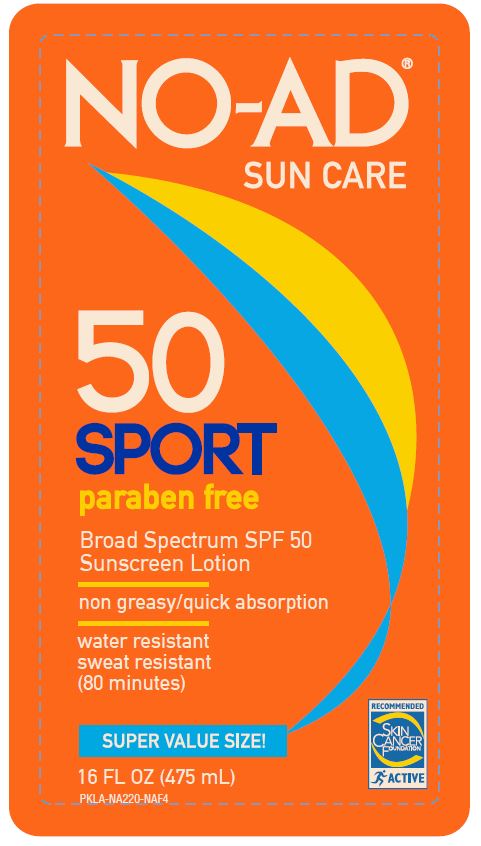 DRUG LABEL: NOAD SPORT SPF 50
NDC: 70281-183 | Form: LOTION
Manufacturer: Solskyn Personal Care LLC
Category: otc | Type: HUMAN OTC DRUG LABEL
Date: 20191008

ACTIVE INGREDIENTS: AVOBENZONE 2.5 g/100 g; OCTISALATE 5 g/100 g; HOMOSALATE 10 g/100 g; OCTOCRYLENE 5 g/100 g; OXYBENZONE 6 g/100 g
INACTIVE INGREDIENTS: METHACRYLIC ACID - ETHYL ACRYLATE COPOLYMER (4500 MPA.S); ALKYL (C12-15) BENZOATE; CARBOMER HOMOPOLYMER, UNSPECIFIED TYPE; ETHYLHEXYL PALMITATE; GLYCERIN; 2-HYDROXYPROPYL METHACRYLATE; PHENOXYETHANOL; COCOA BUTTER; ALPHA-TOCOPHEROL ACETATE; TROLAMINE; ALOE VERA LEAF; SORBITAN MONOOLEATE; EDETATE DISODIUM ANHYDROUS; ETHYLHEXYLGLYCERIN; WATER

NO-AD Sport SPF 50 Lotion

Active Ingredients

Avobenzone 2.5%

Homosalate 10%

Octisalate 5%

Octocrylene 5%

Oxybenzone 6%

Purpose

Sunscreen

Uses

- Helps prevent sunburn
- If used as directed with other sun protection measures (see Directions), decreases the risk of skin cancer and early skin aging caused by the sun.

Warnings

For external use only

Do not use on damaged or broken skin

When using this product keep out of eyes. Rinse with water to remove.

Stop use and ask a doctor if rash occurs

Keep out of reach of children. If swallowed, get medical help or contact a Poison Control Center right away.

Directions

Apply liberally 15 minutes before sun exposure.

Reapply: • after 80 minutes of swimming or sweating

• Immediately after towel drying

• at least every 2 hours.

Sun Protection Measures. Spending time in the sun increases your risk of skin cancer and early skin aging. To decrease this risk, regularly use a sunscreen with broad spectrum of SPF of 15 or higher and other sun protection measures including:

• limit time in the sun, especially 10a.m.-2a.m.

• wear long-sleeved shirts, pants, hats and sunglasses

•Children under 6 months: Ask a doctor

Inactive Ingredients

Acrylates Copolymer, Acrylates/C10-30 Alkyl Acrylate Crosspolymer, Aloe

Barbadensis Leaf Extract, C12-15 Alkyl Benzoate, Carbomer, Disodium EDTA,

Ethylhexyl Palmitate, Ethylhexylglycerin, Fragrance, Glycerin, Hydroxypropyl

Methylcellulose, Phenoxyethanol, Propylene Glycol, Sorbitan Oleate, Theobroma

Cacao (Cocoa) Seed Butter, Tocopheryl (Vitamin E) Acetate, Triethanolamine, Water

Other Information

• for use on skin only. Avoid contact with fabric.

• protect the product in this container from excessive heat and direct sun

Principal Display Panel

NO-AD

SUN CARE

Sport

50

paraben free

Broad Spectrum SPF 50

Sunscreen Lotion

non greasy/quick absorption

water resistant

sweat resistant

(80 minutes)

SUPER VALUE SIZE!

16 FL OZ (475mL)